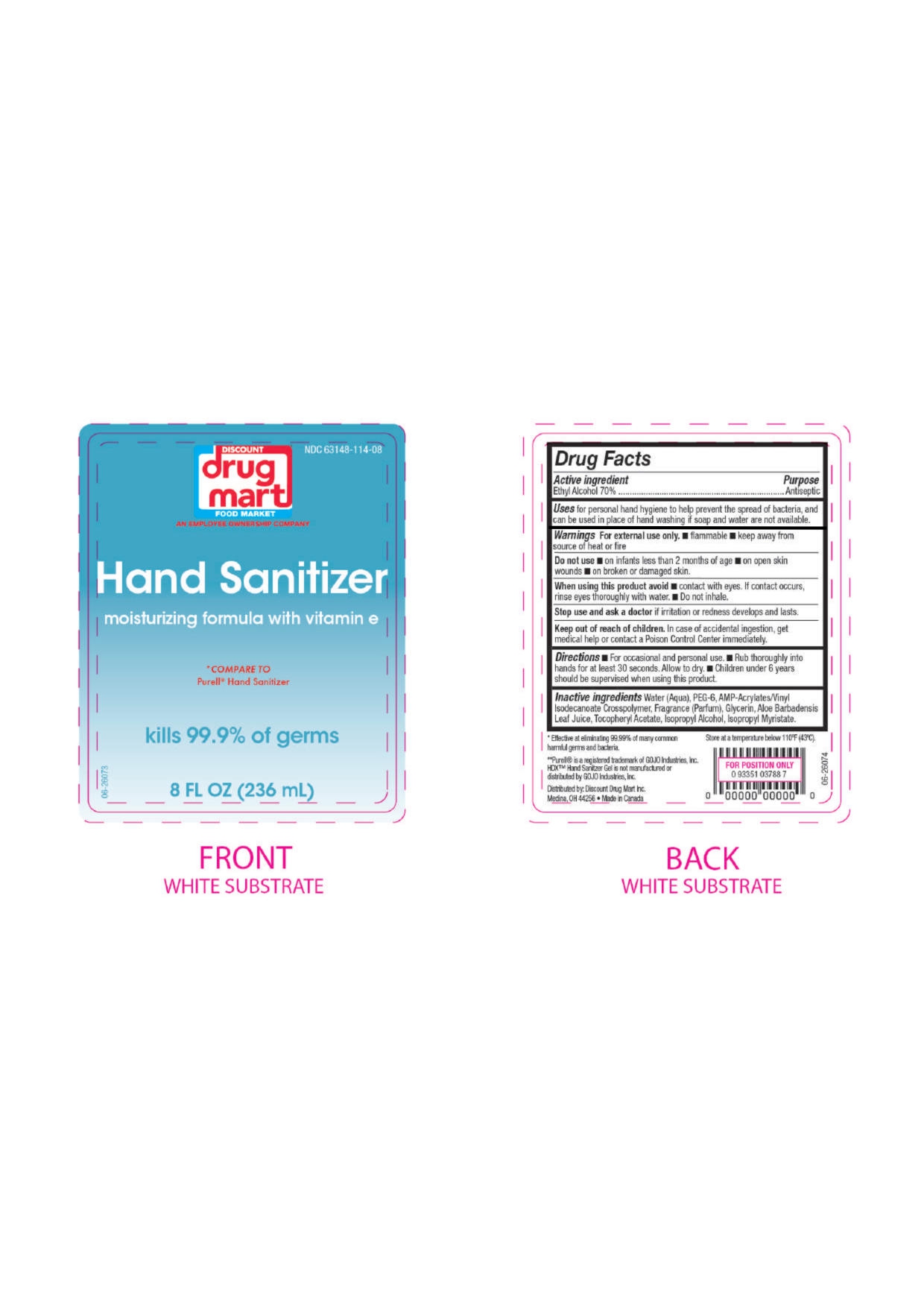 DRUG LABEL: DD Mart Hand Sanitizer
NDC: 63148-114 | Form: LIQUID
Manufacturer: Apollo Health and Beauty Care
Category: otc | Type: HUMAN OTC DRUG LABEL
Date: 20240717

ACTIVE INGREDIENTS: ALCOHOL 70 mL/100 mL
INACTIVE INGREDIENTS: ISOPROPYL ALCOHOL; ACRYLATES/VINYL ISODECANOATE CROSSPOLYMER (10000 MPA.S NEUTRALIZED AT 0.5%); FRAGRANCE CLEAN ORC0600327; .ALPHA.-TOCOPHEROL ACETATE; ISOPROPYL MYRISTATE; POLYETHYLENE GLYCOL 300; GLYCERIN; ALOE VERA LEAF; WATER

NDC- 63148-114-08, DDMart

Active Ingredient

Ethyl Alcohol 70%

Purpose

Antiseptic

Uses

For Personal hand hygiene to help the spread of bacteria and can be used in place of hand washing if soap and water are not available.

Warnings

- For External use only
- Flammable
- Keep away from source of heat or fire.

Do Not use

- on infants less than 2 months of age
- on open skin wounds
- on broken or damaged skin

When using this product

- Avoid contact with eyes. If contact occurs, rinse thoroughly with water.
- Do not Inhale.

Stop use and ask a doctor

If Irritation or redness develops and lasts.

Keep out of reach of children

In case of accidental ingestion, get medical help or contact a Poison Control Centre immediately.

Directions

- For occasional and personal use
- Rub thoroughly into hands for at least 30 seconds. Allow to dry
- Children under 6 years should be supervised when using this product

Inactive Ingredients

Water (Eau), PEG-6, AMP-Acrylates/Vinyl Isodecanoate Crosspolymer, Fragrance (Parfum), Glycerin, Aloe Barbadensis Leaf Juice, Tocopheryl Acetate, Isopropyl Alcohol, Isopropyl Myristate.